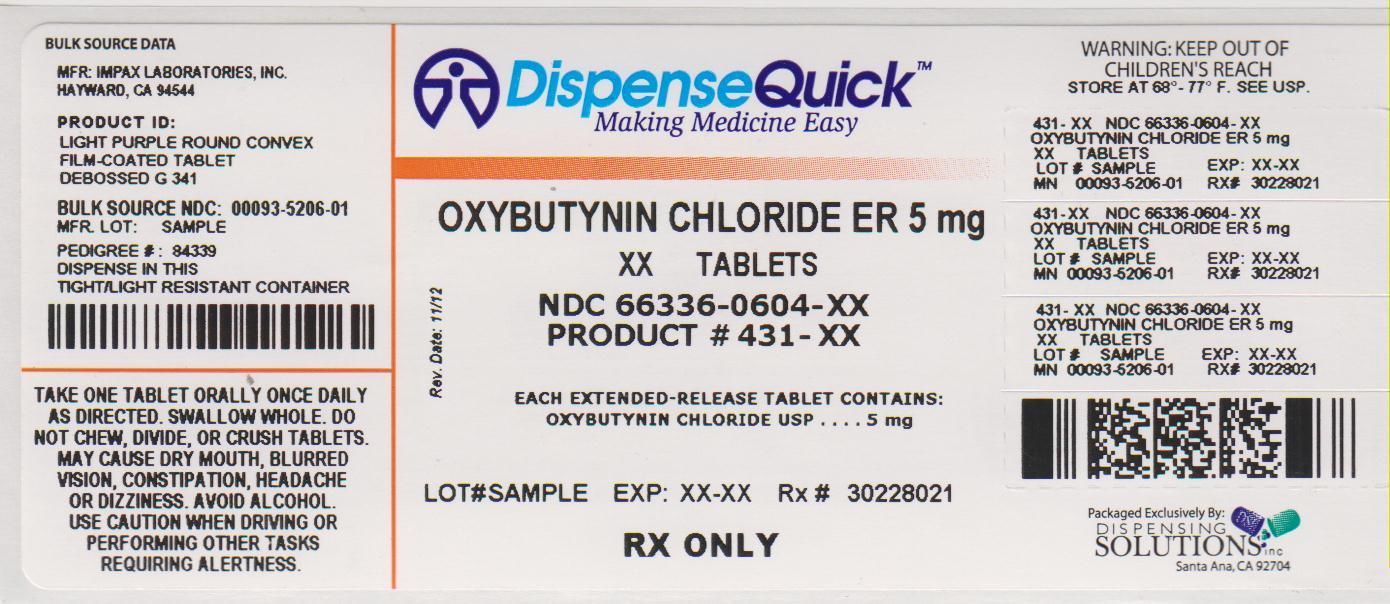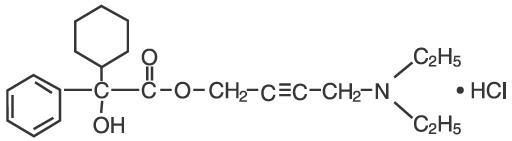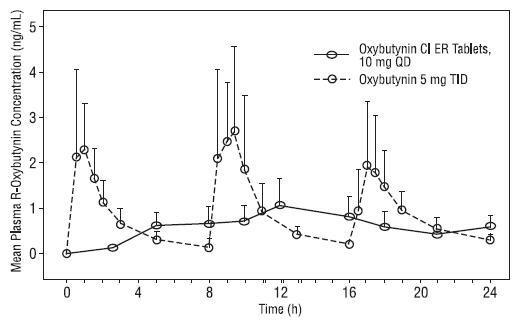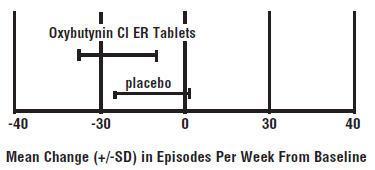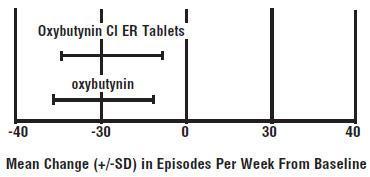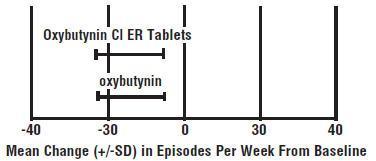 DRUG LABEL: OXYBUTYNIN CHLORIDE
NDC: 66336-604 | Form: TABLET, EXTENDED RELEASE
Manufacturer: Dispensing Solutions, Inc.
Category: prescription | Type: HUMAN PRESCRIPTION DRUG LABEL
Date: 20131030

ACTIVE INGREDIENTS: OXYBUTYNIN CHLORIDE 5 mg/1 1
INACTIVE INGREDIENTS: HYPROMELLOSES; LACTOSE MONOHYDRATE; METHACRYLIC ACID; CELLULOSE, MICROCRYSTALLINE; TALC; TRIETHYL CITRATE; FD&C BLUE NO. 2; FD&C RED NO. 40

OXYBUTYNIN CHLORIDE EXTENDED RELEASE TABLETS,
5 MG, 10 MG AND 15 MG

Rx only

DESCRIPTION

Oxybutynin chloride is an antispasmodic, anticholinergic agent. Each oxybutynin chloride extended release tablet contains 5 mg, 10 mg, or 15 mg of oxybutynin chloride USP, formulated as a once-a-day controlled-release tablet for oral administration. Oxybutynin chloride is administered as a racemate of R- and S- enantiomers.

Chemically, oxybutynin chloride is d,l (racemic) 4-diethylamino- 2-butynyl phenylcyclohexylglycolate hydrochloride. The empirical formula of oxybutynin chloride is C22H31NO3•HCl.

Its structural formula is:

Oxybutynin chloride is a white crystalline solid with a molecular weight of 393.9. It is readily soluble in water and acids, but relatively insoluble in alkalis.

Oxybutynin chloride extended release tablets also contain the following inactive ingredients: hydrogenated vegetable oil, hypromellose, lactose monohydrate, methyacrylic acid copolymer, microcrystalline cellulose, talc and triethyl citrate. The 5 mg tablets contain FD&C Blue No. 2 Aluminum Lake and FD&C Red No. 40 Aluminum Lake. The 10 mg tablets contain FD&C Red No. 40 Aluminum Lake and FD&C Yellow No. 6 Aluminum Lake.

System Components and Performance

Oxybutynin chloride extended release tablets employ an entericcoated hydrophilic hydrogel matrix to deliver oxybutynin chloride at a controlled rate over approximately 24 hours. The system comprises a core, which consists of the drug, rate-controlling hydrogel and other excipients. The core is surrounded by a pH-dependent membrane. In an acidic environment such as the stomach, minimal drug release will occur due to the resistance of the pH-dependent outer membrane. Upon reaching an environment of pH 5.5 and above, the outer membrane dissolves exposing the inner core tablet, which partially hydrates to form a gel layer. Drug release is via slow diffusion out of the gel layer and subsequent gel erosion.

CLINICAL PHARMACOLOGY

Oxybutynin chloride exerts a direct antispasmodic effect on smooth muscle and inhibits the muscarinic action of acetylcholine on smooth muscle. Oxybutynin chloride exhibits only one-fifth of the anticholinergic activity of atropine on the rabbit detrusor muscle, but four to ten times the antispasmodic activity. No blocking effects occur at skeletal neuromuscular junctions or autonomic ganglia (antinicotinic effects).

Oxybutynin chloride relaxes bladder smooth muscle. In patients with conditions characterized by involuntary bladder contractions, cystometric studies have demonstrated that oxybutynin increases bladder (vesical) capacity, diminishes the frequency of uninhibited contractions of the detrusor muscle, and delays the initial desire to void. Oxybutynin thus decreases urgency and the frequency of both incontinent episodes and voluntary urination.

Antimuscarinic activity resides predominantly in the R-isomer. A metabolite, desethyloxybutynin, has pharmacological activity similar to that of oxybutynin in in vitro studies.

Pharmacokinetics

Absorption

Following the first dose of oxybutynin chloride extended release tablets, oxybutynin plasma concentrations rise for 4 to 6 hours; thereafter steady concentrations are maintained for up to 24 hours, minimizing fluctuations between peak and trough concentrations associated with oxybutynin.

The relative bioavailabilities of R- and S-oxybutynin from oxybutynin chloride extended release tablets are 156% and 187%, respectively, compared with oxybutynin. The mean pharmacokinetic parameters for R- and S-oxybutynin are summarized in Table 1. The plasma concentration-time profiles for R- and S-oxybutynin are similar in shape; Figure 1 shows the profile for R-oxybutynin.

Table 1 Mean (SD) R- and S-Oxybutynin Pharmacokinetic Parameters Following a Single Dose of Oxybutynin Chloride Extended Release Tablets 10 mg (n=43)
Parameters (units) | R-Oxybutynin |  | S-Oxybutynin
Cmax (ng/mL) | 1.0 | (0.6) | 1.8 | (1.0)
Tmax (h) | 12.7 | (5.4) | 11.8 | (5.3)
t1/2 (h) | 13.2 | (6.2) | 12.4 | (6.1)
AUC(0 to 48) (ng∙h/mL) | 18.4 | (10.3) | 34.2 | (16.9)
AUCinf (ng∙h/mL) | 21.3 | (12.2) | 39.5 | (21.2)

Figure 1. Mean R-oxybutynin plasma concentrations following a single dose of oxybutynin chloride extended release tablets, 10 mg and oxybutynin 5 mg administered every 8 hours (n=23 for each treatment).

Steady-state oxybutynin plasma concentrations are achieved by Day 3 of repeated oxybutynin chloride extended release tablet dosing, with no observed drug accumulation or change in oxybutynin and desethyloxybutynin pharmacokinetic parameters.

Pharmacokinetic information for pediatric patients 5 to 15 years of age with symptoms of detrusor overactivity associated with a neurological condition (e.g., spina bifida) is approved for Alza Corporation's oxybutynin chloride extended release tablets. However, due to Alza Corporation's marketing exclusivity rights, this drug product is not labeled for pediatric use.

Food Effects

The rate and extent of absorption and metabolism of oxybutynin are similar under fed and fasted conditions.

Distribution

Oxybutynin is widely distributed in body tissues following systemic absorption. The volume of distribution is 193 L after intravenous administration of 5 mg oxybutynin chloride. Both enantiomers of oxybutynin are highly bound (>99%) to plasma proteins. Both enantiomers of N-desethyloxybutynin are also highly bound (>97%) to plasma proteins. The major binding protein is alpha-1 acid glycoprotein.

Metabolism

Oxybutynin is metabolized primarily by the cytochrome P450 enzyme systems, particularly CYP3A4 found mostly in the liver and gut wall. Its metabolic products include phenylcyclohexylglycolic acid, which is pharmacologically inactive, and desethyloxybutynin, which is pharmacologically active. Following oxybutynin chloride extended release tablet administration, plasma concentrations of R- and S-desethyloxybutynin are 73% and 92%, respectively, of concentrations observed with oxybutynin.

Excretion

Oxybutynin is extensively metabolized by the liver, with less than 0.1% of the administered dose excreted unchanged in the urine. Also, less than 0.1% of the administered dose is excreted as the metabolite desethyloxybutynin.

Dose Proportionality

Pharmacokinetic parameters of oxybutynin and desethyloxybutynin (Cmax and AUC) following administration of 5 to 20 mg of oxybutynin chloride extended release tablets are dose proportional.

Special Populations

Geriatric

The pharmacokinetics of oxybutynin chloride extended release tablets were similar in all patients studied (up to 78 years of age).

Pediatric

Pharmacokinetic information for pediatric patients 5 to 15 years of age with symptoms of detrusor overactivity associated with a neurological condition (e.g., spina bifida) is approved for Alza Corporation's oxybutynin chloride extended release tablets. However, due to Alza Corporation's marketing exclusivity rights, this drug product is not labeled for pediatric use.

Gender

There are no significant differences in the pharmacokinetics of oxybutynin in healthy male and female volunteers following administration of oxybutynin chloride extended release tablets.

Race

Available data suggest that there are no significant differences in the pharmacokinetics of oxybutynin based on race in healthy volunteers following administration of oxybutynin chloride extended release tablets.

Renal Insufficiency

There is no experience with the use of oxybutynin chloride extended release tablets in patients with renal insufficiency.

Hepatic Insufficiency

There is no experience with the use of oxybutynin chloride extended release tablets in patients with hepatic insufficiency.

Drug-Drug Interactions

See PRECAUTIONS: Drug Interactions.

CLINICAL STUDIES

Oxybutynin chloride extended release tablets were evaluated for the treatment of patients with overactive bladder with symptoms of urge urinary incontinence, urgency, and frequency in three controlled studies and one open-label study. The majority of patients were Caucasian (89.0%) and female (91.9%) with a mean age of 59 years (range, 18 to 98 years). Entry criteria required that patients have urge or mixed incontinence (with a predominance of urge) as evidenced by ≥ 6 urge incontinence episodes per week and ≥ 10 micturitions per day. Study 1 was a fixed-dose escalation design, whereas the other studies used a dose-adjustment design in which each patient's final dose was adjusted to a balance between improvement of incontinence symptoms and tolerability of side effects. Controlled studies included patients known to be responsive to oxybutynin or other anticholinergic medications, and these patients were maintained on a final dose for up to 2 weeks.

The efficacy results for the three controlled trials are presented in the following tables and figures.

Number of Urge Urinary Incontinence Episodes Per Week
Study 1 | N | Oxybutynin Cl ER Tablets | N | Placebo
Mean Baseline | 34 | 15.9 | 16 | 20.9
Mean (SD) Change from Baseline [Covariate adjusted mean with missing observations set to baseline values] | 34 | -15.8 (8.9) | 16 | -7.6 (8.6)
95% Confidence Interval for Difference | (-13.6,-2.8) [The difference between Oxybutynin Chloride ER Tablets and placebo was statistically significant.]
(Oxybutynin Chloride ER Tablet- Placebo)

Study 2 | N | Oxybutynin Cl ER Tablets | N | Oxybutynin
Mean Baseline | 53 | 27.6 | 52 | 23.0
Mean (SD) Change from Baseline [Covariate adjusted mean with missing observations set to baseline values] | 53 | -17.6 (11.9) | 52 | -19.4 (11.9)
95% Confidence Interval for Difference | (-2.8, 6.5)
(Oxybutynin Chloride ER Tablet- Oxybutynin)

Study 3 | N | Oxybutynin Cl ER Tablets | N | Oxybutynin
Mean Baseline | 111 | 18.9 | 115 | 19.5
Mean (SD) Change from Baseline [Covariate adjusted mean with missing observations set to baseline values] | 111 | -14.5 (8.7) | 115 | -13.8 (8.6)
95% Confidence Interval for Difference | (-3.0, 1.6) [The difference between oxybutynin chloride ER tablets and oxybutynin fulfilled the criteria for comparable efficacy.]
(Oxybutynin Chloride ER Tablet- Oxybutynin)

INDICATIONS AND USAGE

Oxybutynin chloride extended release tablets are once-daily controlled-release tablets indicated for the treatment of overactive bladder with symptoms of urge urinary incontinence, urgency, and frequency.

Pediatric use information for the treatment of patients aged 6 years and older with symptoms of detrusor overactivity associated with a neurological condition (e.g., spina bifida) is approved for Alza Corporation's oxybutynin chloride extended release tablets. However, due to Alza Corporation's marketing exclusivity rights, this drug product is not labeled for pediatric use.

CONTRAINDICATIONS

Oxybutynin chloride extended release tablets are contraindicated in patients with urinary retention, gastric retention and other severe decreased gastrointestinal motility conditions, uncontrolled narrow-angle glaucoma and in patients who are at risk for these conditions.

Oxybutynin chloride extended release tablets are also contraindicated in patients who have demonstrated hypersensitivity to the drug substance or other components of the product.

WARNINGS

Angioedema of the face, lips, tongue and/or larynx has been reported with oxybutynin. In some cases, angioedema occurred after the first dose. Angioedema associated with upper airway swelling may be life-threatening. If involvement of the tongue, hypopharynx, or larynx occurs, oxybutynin should be promptly discontinued and appropriate therapy and/or measures necessary to ensure a patient airway should be promptly provided.

PRECAUTIONS

Central Nervous System Effects

Oxybutynin is associated with anticholinergic central nervous system (CNS) effects (see ADVERSE REACTIONS). A variety of CNS anticholinergic effects have been reported, including hallucinations, agitation, confusion and somnolence. Patients should be monitored for signs of anticholinergic CNS effects, particularly in the first few months after beginning treatment or increasing the dose. If a patient experiences anticholinergic CNS effects, dose reduction or drug discontinuation should be considered.

Oxybutynin chloride extended release tablets should be used with caution in patients with preexisting dementia treated with cholinesterase inhibitors due to the risk of aggravation of symptoms.

General

Oxybutynin chloride extended release tablets should be used with caution in patients with hepatic or renal impairment and in patients with myasthenia gravis due to the risk of symptom aggravation.

Urinary Retention

Oxybutynin chloride extended release tablets should be administered with caution to patients with clinically significant bladder outflow obstruction because of the risk of urinary retention (see CONTRAINDICATIONS).

Gastrointestinal Disorders

Oxybutynin chloride extended release tablets should be administered with caution to patients with gastrointestinal obstructive disorders because of the risk of gastric retention (see CONTRAINDICATIONS).

Oxybutynin chloride extended release tablets, like other anticholinergic drugs, may decrease gastrointestinal motility and should be used with caution in patients with conditions such as ulcerative colitis and intestinal atony.

Oxybutynin chloride extended release tablets should be used with caution in patients who have gastroesophageal reflux and/or who are concurrently taking drugs (such as bisphosphonates) that can cause or exacerbate esophagitis.

As with any other nondeformable material, caution should be used when administering oxybutynin chloride extended release tablets to patients with preexisting severe gastrointestinal narrowing (pathologic or iatrogenic). There have been rare reports of obstructive symptoms in patients with known strictures in association with the ingestion of other drugs in nondeformable controlled-release formulations.

Information for Patients

Patients should be informed that oxybutynin may produce angioedema that could result in life-threatening airway obstruction. Patients should be advised to promptly discontinue oxybutynin therapy and seek immediate medical attention if they experience edema of the tongue, edema of the the laryngopharynx, or difficulty breathing.

Patients should be informed that heat prostration (fever and heat stroke due to decreased sweating) can occur when anticholinergics such as oxybutynin chloride are administered in the presence of high environmental temperature.

Because anticholinergic agents such as oxybutynin may produce drowsiness (somnolence) or blurred vision, patients should be advised to exercise caution.

Patients should be informed that alcohol may enhance the drowsiness caused by anticholinergic agents such as oxybutynin.

Patients should be informed that oxybutynin chloride extended release tablets should be swallowed whole with the aid of liquids. Patients should not chew, divide, or crush tablets.

Oxybutynin chloride extended release tablets should be taken at approximately the same time each day.

Drug Interactions

The concomitant use of oxybutynin with other anticholinergic drugs or with other agents which produce dry mouth, constipation, somnolence (drowsiness), and/or other anticholinergic-like effects may increase the frequency and/or severity of such effects.

Anticholinergic agents may potentially alter the absorption of some concomitantly administered drugs due to anticholinergic effects on gastrointestinal motility. This may be of concern for drugs with a narrow therapeutic index.

Mean oxybutynin chloride plasma concentrations were approximately 2 fold higher when oxybutynin chloride extended release tablets were administered with ketoconazole, a potent CYP3A4 inhibitor. Other inhibitors of the cytochrome P450 3A4 enzyme system, such as antimycotic agents (e.g., itraconazole and miconazole) or macrolide antibiotics (e.g., erythromycin and clarithromycin), may alter oxybutynin mean pharmacokinetic parameters (i.e., Cmax and AUC). The clinical relevance of such potential interactions is not known. Caution should be used when such drugs are co-administered.

Carcinogenesis, Mutagenesis, Impairment of Fertility

A 24-month study in rats at dosages of oxybutynin chloride of 20, 80, and 160 mg/kg/day showed no evidence of carcinogenicity. These doses are approximately 6, 25, and 50 times the maximum human exposure, based on surface area.

Oxybutynin chloride showed no increase of mutagenic activity when tested in Schizosaccharomyces pompholiciformis, Saccharomyces cerevisiae, and Salmonella typhimurium test systems.

Reproduction studies with oxybutynin chloride in the mouse, rat, hamster, and rabbit showed no definite evidence of impaired fertility.

Pregnancy

Teratogenic Effects

Pregnancy Category B

Reproduction studies with oxybutynin chloride in the mouse, rat, hamster, and rabbit showed no definite evidence of impaired fertility or harm to the animal fetus. The safety of oxybutynin chloride extended release tablet administration to women who are or who may become pregnant has not been established. Therefore, oxybutynin chloride extended release tablets should not be given to pregnant women unless, in the judgment of the physician, the probable clinical benefits outweigh the possible hazards.

Nursing Mothers

It is not known whether oxybutynin is excreted in human milk. Because many drugs are excreted in human milk, caution should be exercised when oxybutynin chloride extended release tablets are administered to a nursing woman.

Pediatric Use

Clinical study information for pediatric patients 6 to 15 years of age with symptoms of detrusor overactivity associated with a neurological condition (e.g., spina bifida) is approved for Alza Corporation's oxybutynin chloride extended release tablets. However, due to Alza Corporation's marketing exclusivity rights, this drug product is not labeled for pediatric use.

Oxybutynin chloride extended release tablets are not recommended in pediatric patients who cannot swallow the tablet whole without chewing, dividing, or crushing, or in children under the age of 6 years.

Geriatric Use

The rate and severity of anticholinergic effects reported by patients less than 65 years old and those 65 years and older were similar (see CLINICAL PHARMACOLOGY, Pharmacokinetics, Special Populations: Geriatric).

ADVERSE REACTIONS

Clinical Trials

Because clinical trials are conducted under widely varying conditions, the adverse reaction rates observed in the clinical trials of a drug cannot be directly compared to rates in the clinical trials of another drug and may not reflect the rates observed in clinical practice.

The safety and efficacy of oxybutynin chloride extended-release tablets were evaluated in a total of 580 participants who received oxybutynin chloride extended-release tablets in 4 clinical trials (429 patients) and four pharmacokinetic studies (151 healthy volunteers). The 429 patients were treated with 5 - 30 mg/day for up to 4.5 months. Three of the 4 clinical trials allowed dose adjustments based on efficacy and adverse events and one was a fixed-dose escalation design. Safety information is provided for 429 patients from these three controlled clinical studies and one open-label study in the first column of Table 2 below.

Adverse reactions from two additional fixed-dose, activecontrolled, 12-week treatment duration, postmarketing studies, in which 576 patients were treated with oxybutynin chloride extended-release tablets 10 mg/day, are also listed in Table 2 (second column).

Table 2 Incidence (%) of Adverse Reactions Reported by ≥ 5% of Patients Using Oxybutynin Chloride Extended-Release Tablets (5 – 30 mg/day) and % of Corresponding Adverse Reactions in Two Fixed-Dose (10 mg/day) Studies
Body System | Adverse Reactions | Oxybutynin Chloride ER Tablets | Oxybutynin Chloride ER Tablets
Body System | Adverse Reactions | 5 – 30 mg/day (n = 429) | 10 mg/day (n = 576)
General | headache | 10 | 6
Digestive | dry mouth | 61 | 29
 | constipation | 13 | 7
 | diarrhea | 9 | 7
 | nausea | 9 | 2
 | dyspepsia | 7 | 5
Nervous | somnolence | 12 | 2
 | dizziness | 6 | 4
Special senses | blurred vision | 8 | 1
 | dry eyes | 6 | 3
Urogenital | urinary tract infection | 5 | 5

The most common adverse reactions reported by the 429 patients receiving 5 - 30 mg/day oxybutynin chloride extended-release tablets were the expected side effects of anticholinergic agents. The incidence of dry mouth was dose-related.

The discontinuation rate for all adverse reactions was 6.8% in the 429 patients from the 4 studies of efficacy and safety who received 5-30 mg/day. The most frequent adverse reactions causing early discontinuation of study medication was nausea (1.9%), while discontinuation due to dry mouth was 1.2%.

In addition, the following adverse reactions were reported by ≥ 1 to < 5% of all patients who received oxybutynin chloride extended-release tablets in the 6 adjustable and fixed-dose efficacy and safety studies. Psychiatric disorders: depression, nervousness, insomnia, confusional state; Nervous System Disorders: dysgeusia; Cardiac disorders: palpitations; Vascular disorders: hypertension; Respiratory, thoracic and mediastinal disorders: nasal dryness, cough, oropharyngeal pain, dry throat; Gastrointestinal Disorders: gastroesophageal reflux disease, abdominal pain, flatulence, vomiting; Skin and subcutaneous tissue disorders: dry skin, pruritus; Renal and urinary disorders: urinary retention, urinary hesitation, dysuria; General disorders and administration site conditions: fatigue, edema peripheral, chest pain.

The following adverse reactions were reported by <1% of oxybutynin chloride extended-release tablets-treated patients and at a higher incidence than placebo in clinical trials: Metabolism and Nutrition Disorders: anorexia, fluid retention; Vascular disorders: hot flush; Respiratory, thoracic and mediastinal disorders: dysphonia; Gastrointestinal Disorders: dysphagia, frequent bowel movements; General disorders and administration site conditions: chest discomfort, thirst.

Postmarketing Experience

The following additional adverse drug reactions have been reported from worldwide postmarketing experience with oxybutynin chloride extended-release tablets. Because postmarketing reactions are reported voluntarily from a population of uncertain size, it is not always possible to reliably estimate their frequency or establish a causal relationship to drug exposure.

Psychiatric Disorders: psychotic disorder, agitation, hallucinations, memory impairment; Nervous System Disorders: convulsions; Eye Disorders: glaucoma; Cardiac Disorders: arrhythmia, tachycardia, QT interval prolongation; Vascular Disorders: flushing; Skin and Subcutaneous Tissue Disorders: rash; Renal and Urinary Disorders: impotence; General Disorders and Administration Site Conditions: hypersensitivity reactions, including angioedema with airway obstruction, urticaria, and face edema; rare anaphylactic reactions requiring hospitalization for emergency treatment; Injury, poisoning and procedural complications: fall.

Additional adverse events reported with some other oxybutynin chloride formulations include: cycloplegia, mydriasis, and suppression of lactation.

OVERDOSAGE

The continuous release of oxybutynin from oxybutynin chloride extended release tablets should be considered in the treatment of overdosage. Patients should be monitored for at least 24 hours. Treatment should be symptomatic and supportive. Activated charcoal as well as a cathartic may be administered.

Overdosage with oxybutynin chloride has been associated with anticholinergic effects including central nervous system excitation, flushing, fever, dehydration, cardiac arrhythmia, vomiting, and urinary retention.

Ingestion of 100 mg oxybutynin chloride in association with alcohol has been reported in a 13-year-old boy who experienced memory loss, and a 34-year-old woman who developed stupor, followed by disorientation and agitation on awakening, dilated pupils, dry skin, cardiac arrhythmia, and retention of urine. Both patients fully recovered with symptomatic treatment.

DOSAGE AND ADMINISTRATION

Oxybutynin chloride extended release tablets must be swallowed whole with the aid of liquids, and must not be chewed, divided, or crushed.

Oxybutynin chloride extended release tablets may be administered with or without food.

Adults

The recommended starting dose of oxybutynin chloride extended release tablets is 5 or 10 mg once daily at approximately the same time each day. Dosage may be adjusted in 5-mg increments to achieve a balance of efficacy and tolerability (up to a maximum of 30 mg/day). In general, dosage adjustment may proceed at approximately weekly intervals.

Pediatric patients

Dosing information for pediatric patients aged 6 years and older is approved for Alza Corporation's oxybutynin chloride extended release tablets. However, due to Alza Corporation's marketing exclusivity rights, this drug product is not labeled for pediatric use.

HOW SUPPLIED

Oxybutynin chloride extended-release tablets, 5 mg – Each light purple, film-coated, round convex tablets, debossed with "G 341" on one side and plain on the other side

Bottles of 100 NDC 0093-5206-01

Oxybutynin chloride extended-release tablets, 10 mg – Each light pink, film-coated, round convex tablets, debossed with "G 342" on one side and plain on the other side

Bottles of 100 NDC 0093-5207-01

Oxybutynin chloride extended-release tablets, 15 mg – Each off-white, film-coated, round convex tablets, debossed with "G 343" on one side and plain on the other side

Bottles of 100 NDC 0093-5208-01

Storage

Store at 20°C to 25°C (68°F to 77°F) [see USP Controlled Room Temperature]. Protect from moisture and humidity.

Dispense in a tightly-closed, light-resistant container (USP).

Manufactured By:
IMPAX Laboratories, Inc.
Hayward, CA 94544 USA

Manufactured For:
TEVA PHARMACEUTICALS USA
Sellersville, PA 18960

Rx only

Rev. 11/2012
675-03

PRINCIPAL DISPLAY PANEL - 5 mg Tablet Bottle Label

NDC 66336-0604-XX

NDC 66336-0604-30